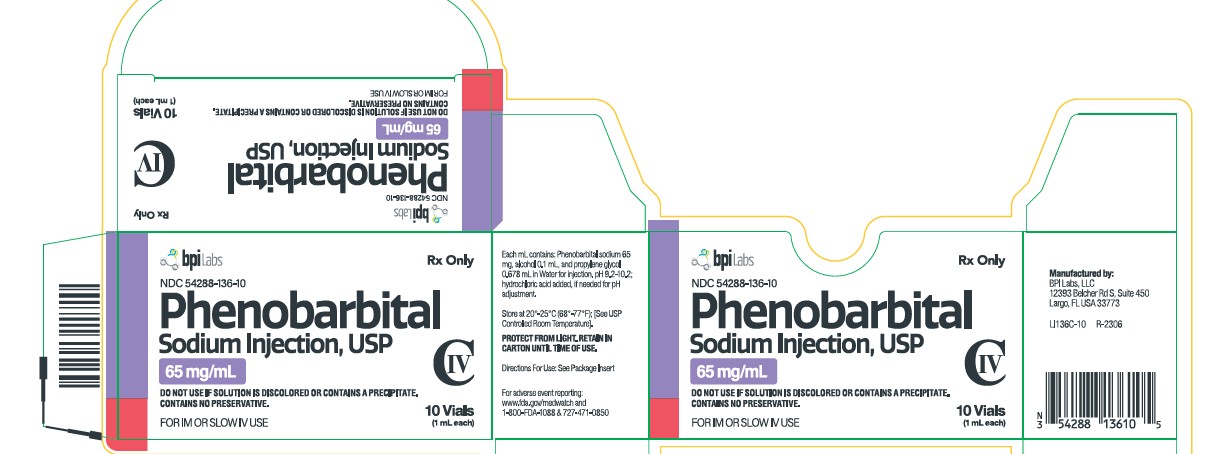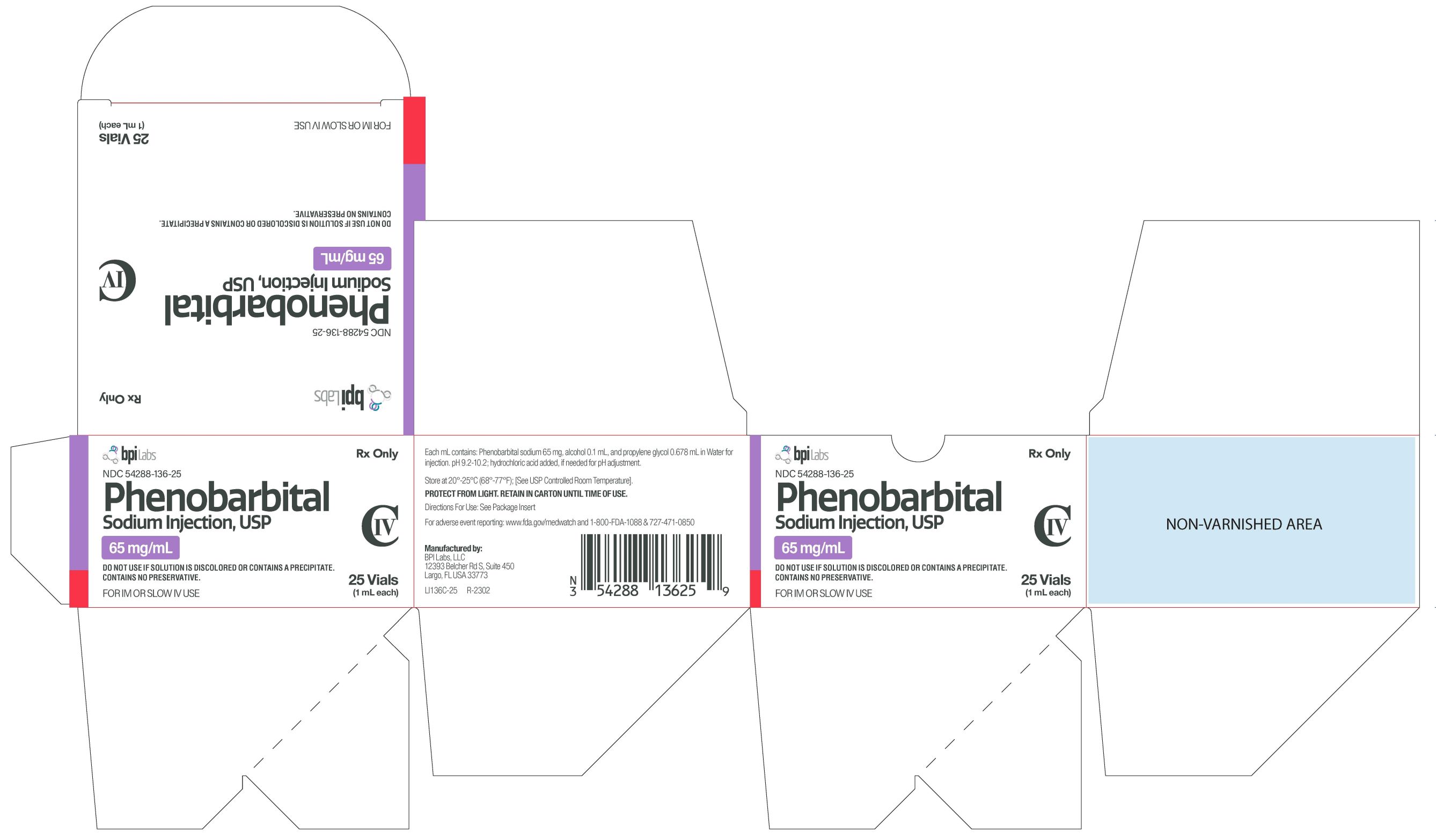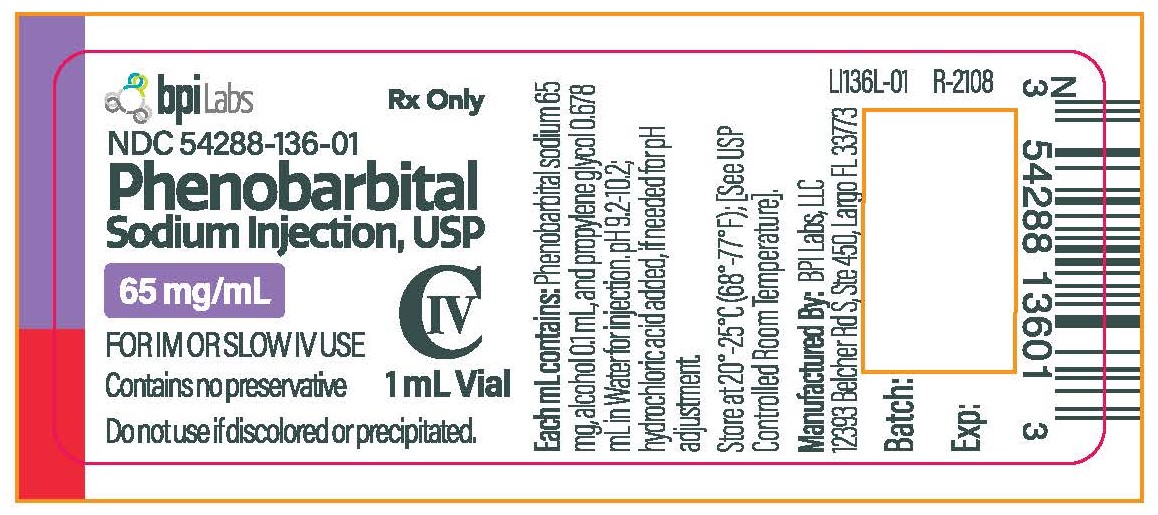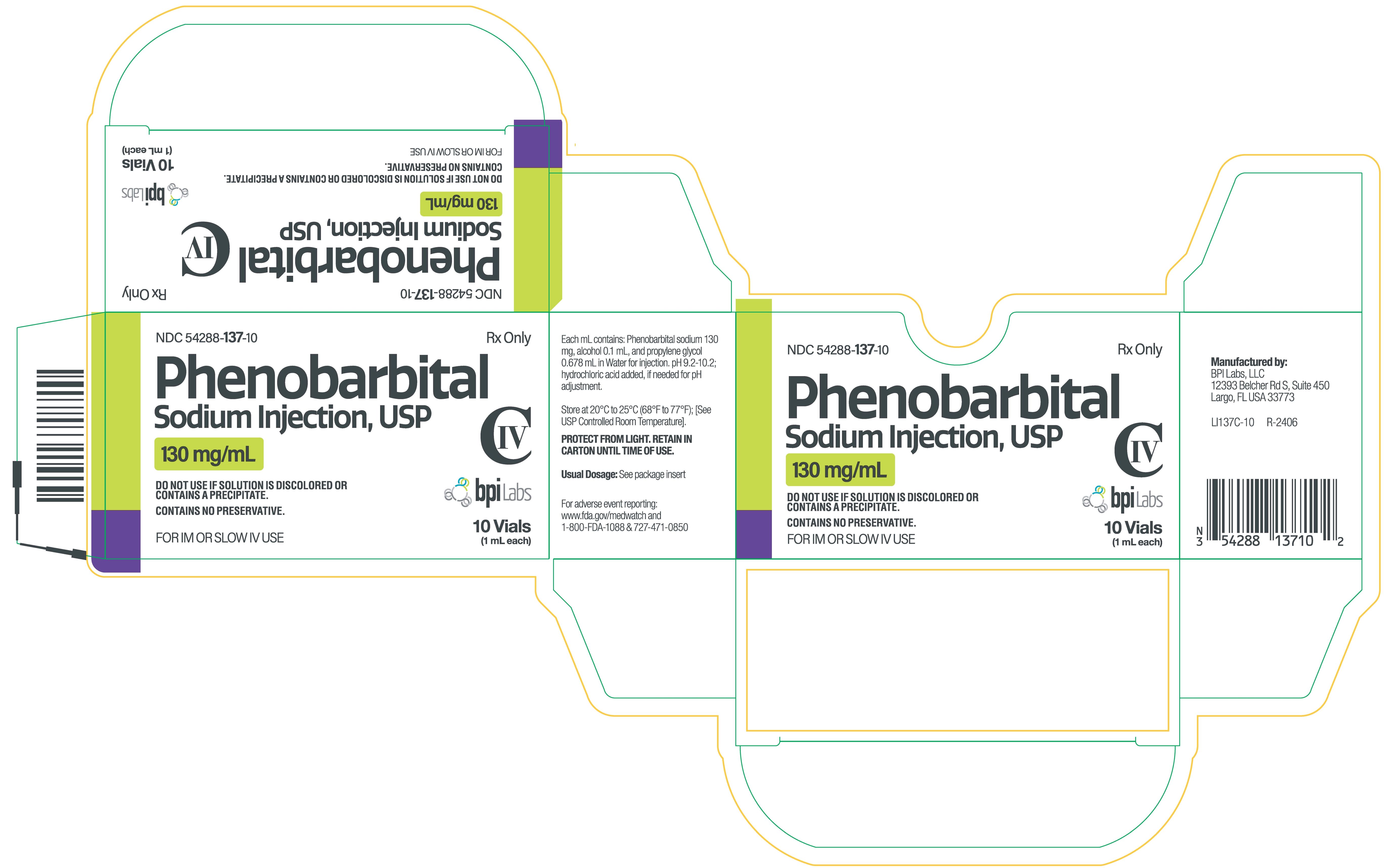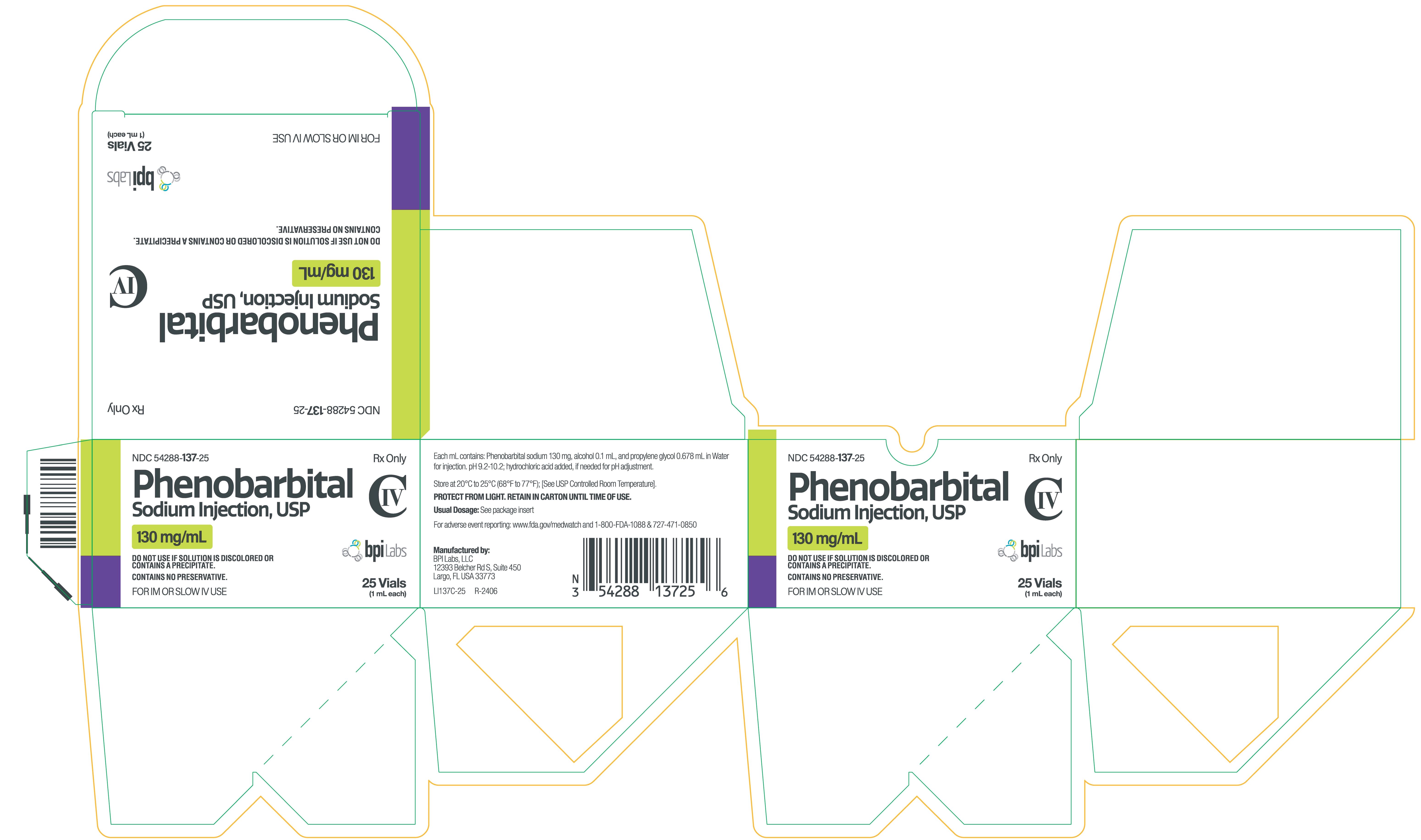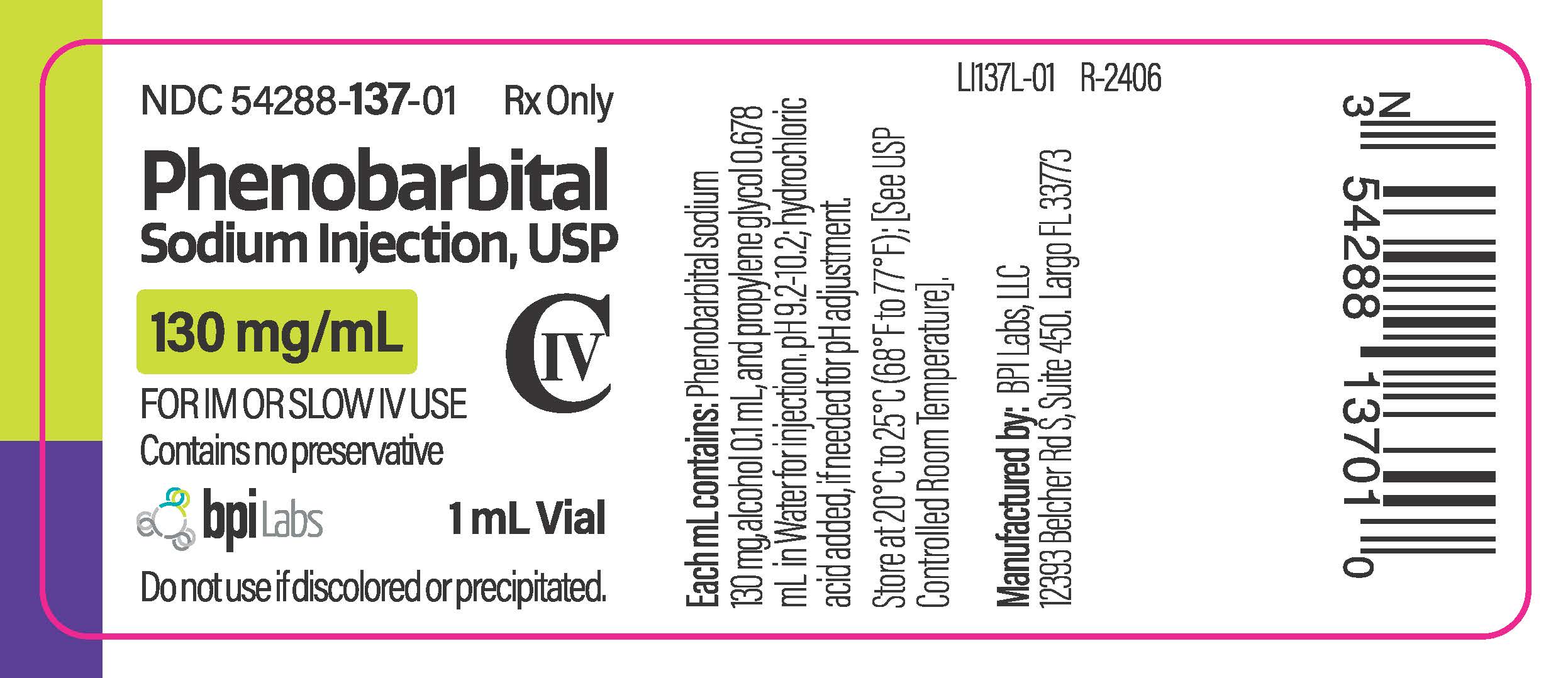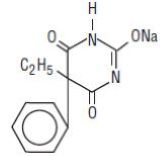 DRUG LABEL: Phenobarbital Sodium
NDC: 54288-136 | Form: INJECTION
Manufacturer: BPI Labs LLC
Category: prescription | Type: HUMAN PRESCRIPTION DRUG LABEL
Date: 20251217
DEA Schedule: CIV

ACTIVE INGREDIENTS: PHENOBARBITAL SODIUM 65 mg/1 mL
INACTIVE INGREDIENTS: ALCOHOL 0.1 mL/1 mL; PROPYLENE GLYCOL 0.678 mL/1 mL; WATER; HYDROCHLORIC ACID

Phenobarbital Sodium Injection, USP
CIV
FOR IM OR SLOW IV ADMINISTRATION ONLY
DO NOT USE IF SOLUTION IS DISCOLORED OR CONTAINS A PRECIPITATE
Rx only

DESCRIPTION

The barbiturates are nonselective central nervous system (CNS) depressants which are primarily used as sedative hypnotics and also anticonvulsants in subhypnotic doses. The barbiturates and their sodium salts are subject to control under the Federal Controlled Substances Act (CIV).

Barbiturates are substituted pyrimidine derivatives in which the basic structure common to these drugs is barbituric acid, a substance which has no central nervous system activity. CNS activity is obtained by substituting alkyl, alkenyl or aryl groups on the pyrimidine ring.

Phenobarbital Sodium Injection, USP is a sterile solution for intramuscular or slow intravenous administration as a long-acting barbiturate. Each mL contains phenobarbital sodium either 65 mg or 130 mg, alcohol 0.1 mL, and propylene glycol 0.678 mL in Water for Injection; hydrochloric acid added, if needed, for pH adjustment. The pH range is 9.2-10.2. Contains no preservative.

Chemically, phenobarbital sodium is 2,4,6(1 H,3 H,5 H)-Pyrimidinetrione,5-ethyl-5-phenyl-, monosodium salt and has the following structural formula:

C12H11N2NaO3 MW 254.22

The sodium salt of phenobarbital occurs as a white, slightly bitter powder, crystalline granules or flaky crystals; it is soluble in alcohol and practically insoluble in ether or chloroform.

CLINICAL PHARMACOLOGY

Barbiturates are capable of producing all levels of CNS mood alteration from excitation to mild sedation, to hypnosis and deep coma. Overdosage can produce death. In high enough therapeutic doses, barbiturates induce anesthesia.

Barbiturates depress the sensory cortex, decrease motor activity, alter cerebellar function and produce drowsiness, sedation and hypnosis.

Barbiturate-induced sleep differs from physiological sleep. Sleep laboratory studies have demonstrated that barbiturates reduce the amount of time spent in the rapid eye movement (REM) phase of sleep or dreaming stage. Also, Stages III and IV sleep are decreased. Following abrupt cessation of barbiturates used regularly, patients may experience markedly increased dreaming, nightmares and/or insomnia. Therefore, withdrawal of a single therapeutic dose over 5 or 6 days has been recommended to lessen the REM rebound and disturbed sleep which contribute to drug withdrawal syndrome (for example, decrease the dose from 3 to 2 doses a day for 1 week).

In studies, secobarbital sodium and pentobarbital sodium have been found to lose most of their effectiveness for both inducing and maintaining sleep by the end of 2 weeks of continued drug administration even with the use of multiple doses. As with secobarbital sodium and pentobarbital sodium, other barbiturates might be expected to lose their effectiveness for inducing and maintaining sleep after about 2 weeks. The short-, intermediate- and, to a lesser degree, long-acting barbiturates have been widely prescribed for treating insomnia. Although the clinical literature abounds with claims that the short-acting barbiturates are superior for producing sleep while the intermediate-acting compounds are more effective in maintaining sleep, controlled studies have failed to demonstrate these differential effects. Therefore, as sleep medications, the barbiturates are of limited value beyond shortterm use.

Barbiturates have little analgesic action at subanesthetic doses. Rather, in subanesthetic doses these drugs may increase the reaction to painful stimuli. All barbiturates exhibit anticonvulsant activity in anesthetic doses.

Barbiturates are respiratory depressants by virtue of their direct effect on the medullary respiratory center. They diminish and, in high doses, may abolish the sensitivity of the respiratory center to its normal stimulus, carbon dioxide. The degree of respiratory depression is dependent upon dose. With hypnotic doses, respiratory depression produced by barbiturates is similar to that which occurs during physiologic sleep with slight decrease in blood pressure and heart rate.

Ordinary hypnotic doses of barbiturates have no significant effect on the cardiovascular system. The barbiturates tend to decrease the tonus of the gastrointestinal musculature. They have no direct injurious effect on the normal kidney. Severe oliguria or anuria may occur in acute barbiturate poisoning, largely as a result of the marked hypotension.

Hypnotic doses tend to reduce slightly the metabolic rate in man. Body temperature is reduced slightly, owing to lessened activity and to depression of the central temperature-regulatory mechanisms.

While anesthetic doses of all barbiturates exert an anticonvulsant effect, phenobarbital has a selective anticonvulsant activity independent of the degree of sedation produced. Phenobarbital limits the spread of seizures and raises the seizure threshold in grand mal (generalized tonic-clonic) epilepsy.

Studies in laboratory animals have shown that barbiturates cause reduction in the tone and contractility of the uterus, ureters and urinary bladder. However, concentrations of the drugs required to produce this effect in humans are not reached with sedative-hypnotic doses.

Barbiturates do not impair normal hepatic function, but have been shown to induce liver microsomal enzymes, thus increasing and/or altering the metabolism of barbiturates and other drugs. (See PRECAUTIONS, Drug Interactions .)

Following IV administration, the onset of action is 5 minutes for phenobarbital sodium. For IM administration, the onset of action is slightly slower. Maximal CNS depression may not occur until 15 minutes or more after IV administration.

Duration of action, which is related to the rate at which the barbiturates are redistributed throughout the body, varies among persons and in the same person from time to time.

No studies have demonstrated that the different routes of administration are equivalent with respect to bioavailability.

Barbiturates are weak acids that are absorbed and rapidly distributed to all tissues and fluids with high concentrations in the brain, liver and kidneys. Lipid solubility of the barbiturates is the dominant factor in their distribution within the body. The more lipid soluble the barbiturate, the more rapidly it penetrates all tissues of the body. Barbiturates are bound to plasma and tissue proteins to a varying degree with the degree of binding increasing directly as a function of lipid solubility.

Phenobarbital has the lowest lipid solubility, lowest plasma binding, lowest brain protein binding, the longest delay in onset of activity and the longest duration of action. Its diffusion across the blood-brain barrier and its distribution into other tissues occurs more slowly than with other short-acting barbiturates. Fifteen minutes or more may be required for maximal central depression following intravenous administration of phenobarbital. However, with time, phenobarbital distributes into all tissues and fluids. Barbiturates are known to cross the placenta. Phenobarbital is 20-45% protein bound. In adults, the plasma half-life of phenobarbital is 53 to 118 hours (mean 79 hours) and in children/newborns, the plasma half-life is 60 to 180 hours (mean 110 hours).

Barbiturates are metabolized primarily by the hepatic microsomal enzyme system, and the metabolic products are excreted in the urine and, less commonly, in the feces. Approximately 25 to 50 percent of a dose of phenobarbital is eliminated unchanged in the urine, whereas the amount of other barbiturates excreted unchanged in the urine is negligible. Urinary pH and rate of urine flow affect the renal circulation of unchanged phenobarbital, a greater quantity being eliminated in alkaline urine and at increased flow rates. The excretion of unmetabolized barbiturate is one feature that distinguishes the long-acting category from those belonging to other categories which are almost entirely metabolized. The inactive metabolites of the barbiturates are excreted as conjugates of glucuronic acid.

INDICATIONS AND USAGE

Parenteral

1. Sedative. Sedation is obtainable within an hour, and in adequate dosage, the duration of action is more than six hours. Included in the more common conditions in which the sedative action of this class of drugs is desired are anxiety-tension states, hyperthyroidism, essential hypertension, nausea and vomiting of functional origin, motion sickness, acute labyrinthitis, pylorospasm in infants, chorea and cardiac failure. Phenobarbital is also a useful adjunct in treatment of hemorrhage from the respiratory or gastrointestinal tract. Phenobarbital controls anxiety, decreases muscular activity and lessens nervous excitability in hyperthyroid patients. However, thyrotoxic individuals occasionally react poorly to barbiturates.
2. Hypnotic, for the short-term treatment of insomnia, since it appears to lose its effectiveness for sleep induction and sleep maintenance after 2 weeks (see CLINICAL PHARMACOLOGY).
3. Preanesthetic.
4. Long-term anticonvulsant, (phenobarbital, mephobarbital and metharbital) for the treatment of generalized tonic-clonic and cortical focal seizures. And, in the emergency control of certain acute convulsive episodes, e.g., those associated with status epilepticus, cholera, eclampsia, cerebral hemorrhage, meningitis, tetanus, and toxic reactions to strychnine or local anesthetics. Phenobarbital sodium may be administered intramuscularly or intravenously as an anticonvulsant for emergency use. When administered intravenously, it may require 15 or more minutes before reaching peak concentrations in the brain. Therefore, injecting phenobarbital sodium until the convulsions stop may cause the brain level to exceed that required to control the convulsions and lead to severe barbiturate-induced depression.
5. Phenobarbital is indicated in pediatric patients as an anticonvulsant and as a sedative, including its preoperative and postoperative use.

CONTRAINDICATIONS

Barbiturates are contraindicated in patients with known barbiturate sensitivity. Barbiturates are also contraindicated in patients with a history of manifest or latent porphyria, marked impairment of liver functions or with severe respiratory distress where dyspnea or obstruction is evident. Large doses are contraindicated in nephritic subjects.

Barbiturates should not be administered to persons with known previous addiction to the sedative-hypnotic group since ordinary doses may be ineffectual and may contribute to further addiction.

Intraarterial administration is contraindicated. Its consequences vary from transient pain to gangrene. Subcutaneous administration produces tissue irritation, ranging from tenderness and redness to necrosis and is not recommended. (See DOSAGE AND ADMINISTRATION, Treatment of Adverse Effects Due to Inadvertent Error in Administration.)

WARNINGS

Habit Forming

Barbiturates may be habit forming. Tolerance and psychological and physical dependence may occur with continued use (see DRUG ABUSE AND DEPENDENCEand CLINICAL PHARMACOLOGY). Patients who are psychologically dependent on barbiturates may increase the dosage or decrease the dosage interval without consulting a physician and may subsequently develop a physical dependence on barbiturates. To minimize the possibility of overdosage or the development of dependence, the prescribing and dispensing of sedative-hypnotic barbiturates should be limited to the amount required for the interval until the next appointment. Abrupt cessation after prolonged use in the dependent person may result in withdrawal symptoms, including delirium, convulsions and possibly death. Barbiturates should be withdrawn gradually from any patient known to be taking excessive dosage over long periods of time (see DRUG ABUSE AND DEPENDENCE).

Dermatologic Reactions

Exfoliative dermatitis and Stevens-Johnson syndrome, possibly fatal, are rare hypersensitivity reactions to phenobarbital. Physicians should be alert to signs which may precede the onset of barbiturate-induced cutaneous lesions, and the drug should be discontinued whenever dermatological reactions occur.

Intravenous Administration

Too rapid administration may cause severe respiratory depression, apnea, laryngospasm, hypertension or vasodilation with fall in blood pressure.

When administered intravenously, it may require 15 or more minutes before reaching peak concentrations in the brain. Therefore, injecting phenobarbital sodium until the convulsions stop may cause brain levels to exceed that required to control the convulsions and lead to severe barbiturate-induced depression.

Acute or Chronic Pain

Caution should be exercised when barbiturates are administered to patients with acute or chronic pain, because paradoxical excitement could be induced or important symptoms could be masked. However, the use of barbiturates as sedatives in the postoperative surgical period and as adjuncts to cancer chemotherapy is well established.

Use in Pregnancy

Barbiturates can cause fetal harm when administered to a pregnant woman. Retrospective, case-controlled studies have suggested a connection between the maternal consumption of barbiturates and a higher than expected incidence of fetal abnormalities. Phenobarbital may cause major fetal malformations.

Following oral or parenteral administration, barbiturates readily cross the placental barrier and are distributed throughout fetal tissues with highest concentrations found in the placenta, fetal liver and brain. Fetal blood levels approach maternal blood levels following parenteral administration.

Withdrawal symptoms occur in infants born to mothers who receive barbiturates throughout the last trimester of pregnancy (see DRUG ABUSE AND DEPENDENCE).

Phenobarbital should be used during pregnancy only when clearly indicated. If phenobarbital is used during pregnancy or if the patient becomes pregnant while taking the drug, the patient should be apprised of the potential hazard to the fetus.

Use in Children

Phenobarbital has been reported to be associated with cognitive defects in children taking it for complicated febrile seizures.

Synergistic Effects

The concomitant use of alcohol or other CNS depressants may produce additive CNS depressant effects.

PRECAUTIONS

General

Untoward reactions may occur in the presence of fever, hyperthyroidism, diabetes mellitus and severe anemia. In cases of great debility, severely impaired liver function, pulmonary or cardiac disease, status asthmaticus, shock or uremia, phenobarbital sodium should be used with extreme caution. Intramuscular injection should be confined to a total volume of 5 mL and made in a large muscle in order to avoid possible tissue irritation.

Barbiturates may be habit forming. Tolerance and psychological and physical dependence may occur with continued use (see DRUG ABUSE AND DEPENDENCE). Barbiturates should be administered with caution, if at all, to patients who are mentally depressed, have suicidal tendencies or a history of drug abuse.

Elderly or debilitated patients may react to barbiturates with marked excitement, depression and confusion. In some persons, barbiturates repeatedly produce excitement rather than depression.

In patients with hepatic damage, barbiturates should be administered with caution and initially in reduced doses. Barbiturates should not be administered to patients showing the premonitory signs of hepatic coma.

Parenteral solutions of barbiturates are highly alkaline. Therefore, extreme care should be taken to avoid perivascular extravasation or intraarterial injection. Extravascular injection may cause local tissue damage with subsequent necrosis; consequences of intraarterial injection may vary from transient pain to gangrene of the limb. Any complaint of pain in the limb warrants stopping the injection.

Information for the Patient

Practitioners should give the following information and instructions to patients receiving barbiturates:

1. The use of barbiturates carries with it an associated risk of psychological and/or physical dependence. The patient should be warned against increasing the dose of the drug without consulting a physician.
2. Barbiturates may impair mental and/or physical abilities required for the performance of potentially hazardous tasks (e.g., driving, operating machinery, etc.).
3. Alcohol should not be consumed while taking barbiturates. Concurrent use of the barbiturates with other CNS depressants (e.g., alcohol, narcotics, tranquilizers and antihistamines) may result in additional CNS depressant effects.
4. If phenobarbital is used during pregnancy, the patient should be apprised of the potential hazard to the fetus (see WARNINGS).

Drug Interactions

Most reports of clinically significant drug interactions occurring with the barbiturates have involved phenobarbital. However, the application of these data to other barbiturates appears valid and warrants serial blood level determinations of the relevant drugs when there are multiple therapies.

Anticoagulants

Phenobarbital lowers the plasma levels of dicumarol (bishydroxycoumarin) and causes a decrease in anticoagulant activity as measured by the prothrombin time. Barbiturates can induce hepatic microsomal enzymes resulting in increased metabolism and decreased anticoagulant response of oral anticoagulants (e.g., warfarin, acenocoumarol, dicumarol and phenprocoumon). Patients stabilized on anticoagulant therapy may require dosage adjustments if barbiturates are added to or withdrawn from their dosage regimen.

Corticosteroids

Barbiturates appear to enhance the metabolism of exogenous corticosteroids probably through the induction of hepatic microsomal enzymes. Patients stabilized on corticosteroid therapy may require dosage adjustments if barbiturates are added to or withdrawn from their dosage regimen.

Griseofulvin

Phenobarbital appears to interfere with the absorption of orally administered griseofulvin, thus decreasing its blood level. The effect of the resultant decreased blood levels of griseofulvin on therapeutic response has not been established. However, it would be preferable to avoid concomitant administration of these drugs.

Doxycycline

Phenobarbital has been shown to shorten the half-life of doxycycline for as long as 2 weeks after barbiturate therapy is discontinued. This mechanism is probably through the induction of hepatic microsomal enzymes that metabolize the antibiotic. If phenobarbital and doxycycline are administered concurrently, the clinical response to doxycycline should be monitored closely.

Phenytoin, Sodium Valproate, Valproic Acid

The effect of barbiturates on the metabolism of phenytoin appears to be variable. Some investigators report an accelerating effect, while others report no effect. Because the effect of barbiturates on the metabolism of phenytoin is not predictable, phenytoin and barbiturate blood levels should be monitored more frequently if these drugs are given concurrently. Sodium valproate and valproic acid appear to decrease barbiturate metabolism; therefore, barbiturate blood levels should be monitored and appropriate dosage adjustments made as indicated.

Central Nervous System Depressants

The concomitant use of other central nervous system depressants, including other sedatives or hypnotics, antihistamines, tranquilizers or alcohol, may produce additive depressant effects.

Monoamine Oxidase Inhibitors (MAOIs)

MAOIs prolong the effects of barbiturates probably because metabolism of the barbiturate is inhibited.

Estradiol, Estrone, Progesterone and Other Steroidal Hormones

Pretreatment with or concurrent administration of phenobarbital may decrease the effect of estradiol by increasing its metabolism. There have been reports of patients treated with antiepileptic drugs (e.g., phenobarbital) who became pregnant while taking oral contraceptives. An alternate contraceptive method might be suggested to women taking phenobarbital.

Drug/Laboratory Test Interactions

Prolonged therapy with barbiturates should be accompanied by periodic laboratory evaluation of organ systems, including hematopoietic, renal and hepatic systems (see PRECAUTIONS, General and ADVERSE REACTIONS).

Carcinogenesis, Mutagenesis, Impairment of Fertility

Animal Data

Phenobarbital sodium is carcinogenic in mice and rats after lifetime administration. In mice, it produced benign and malignant liver-cell tumors. In rats, benign liver-cell tumors were observed very late in life.

Human Data

In an epidemiological study of 9,136 patients who were treated on an anticonvulsant protocol which included phenobarbital, results indicated a higher than normal incidence of hepatic carcinoma.

Previously, some of these patients were treated with thorotrast, a drug which is known to produce hepatic carcinomas. Thus, this study did not provide sufficient evidence that phenobarbital is carcinogenic in humans. A retrospective study of 84 children with brain tumors matched to 73 normal controls and 78 cancer controls (malignant disease other than brain tumors) suggested an association between exposure to barbiturates prenatally and an increased incidence of brain tumors.

Pregnancy

Teratogenic Effects-Pregnancy Category D

Phenobarbital may cause major fetal malformations. (See WARNINGS, Use in Pregnancy.)

Nonteratogenic Effects

Reports of infants suffering from long-term barbiturate exposure in uteroincluded the acute withdrawal syndrome of seizures and hyperirritability from birth to a delayed onset of up to 14 days. (See DRUG ABUSE AND DEPENDENCE.)

Labor and Delivery

Hypnotic doses of barbiturates do not appear to significantly impair uterine activity during labor. Full anesthetic doses of barbiturates decrease the force and frequency of uterine contractions. Administration of sedative-hypnotic barbiturates to the mother during labor may result in respiratory depression in the newborn. Premature infants are particularly susceptible to the depressant effects of barbiturates. If barbiturates are used during labor and delivery, resuscitation equipment should be available.

Barbiturates are additive with other central nervous system depressants administered during labor and delivery. Data are currently not available to evaluate the effect of barbiturates when forceps delivery or other intervention is necessary or to determine the long-term effects of obstetrically administered barbiturates on the later growth, development and functional maturation of the child.

While barbiturates are usually reported to have a minimal effect on neonatal behavior, a delayed interest in breastfeeding and a depressed response to auditory and visual stimuli have been noted.

Nursing Mothers

Caution should be exercised when a barbiturate is administered to a nursing woman since small amounts of barbiturates are excreted in the milk.

ADVERSE REACTIONS

The following adverse reactions and their incidence were compiled from surveillance of thousands of hospitalized patients. Because such patients may be less aware of certain of the milder adverse effects of barbiturates, the incidence of these reactions may be somewhat higher in fully ambulatory patients.

Nervous System

Somnolence, agitation, confusion, hyperkinesia, ataxia, CNS depression, nightmares, nervousness, psychiatric disturbance, hallucinations, insomnia, anxiety, dizziness, thinking abnormality

Respiratory System

Hypoventilation, apnea

Cardiovascular System

Bradycardia, hypotension, syncope

Digestive System

Nausea, vomiting, constipation

Dermatologic Reactions

Exfoliative dermatitis, Stevens-Johnson syndrome, toxic epidermic necrolysis.

Other Reported Reactions

Headache; injection site reactions; hypersensitivity reactions, including but not limited to angioedema and skin rashes; fever; liver damage and megaloblastic anemia following chronic phenobarbital use.

DRUG ABUSE AND DEPENDENCE

Phenobarbital Sodium Injection is a Schedule IV controlled substance.

Barbiturates may be habit forming. Tolerance and psychological dependence and physical dependence may occur especially following prolonged use of high doses of barbiturates. As tolerance to barbiturates develops, the amount needed to maintain the same level of intoxication increases; tolerance to a fatal dosage, however, does not increase more than two-fold. As this occurs, the margin between an intoxicating dosage and fatal dosage becomes smaller. Symptoms of acute intoxication with barbiturates include unsteady gait, slurred speech and sustained nystagmus. Mental signs of chronic intoxication include confusion, poor judgment, irritability, insomnia and somatic complaints. Symptoms of barbiturate dependence are similar to those of chronic alcoholism. If an individual appears to be intoxicated with alcohol to a degree that is radically disproportionate to the amount of alcohol in his or her blood, the use of barbiturates should be suspected. The lethal dose of a barbiturate is far less if alcohol is also ingested.

The symptoms of barbiturate withdrawal can be severe and may cause death. Minor withdrawal symptoms may appear 8 to 12 hours after the last dose of a barbiturate. These symptoms usually appear in the following order: anxiety, muscle twitching, tremor of hands and fingers, progressive weakness, dizziness, distortion in visual perception, nausea, vomiting, insomnia and orthostatic hypotension. Major withdrawal symptoms (convulsions and delirium) may occur within 16 hours and last up to 5 days after abrupt cessation of these drugs. Intensity of withdrawal symptoms gradually declines over a period of approximately 15 days. Individuals susceptible to barbiturate abuse and dependence include alcoholics and opiate abusers, as well as other sedative-hypnotic and amphetamine abusers.

Drug dependence to barbiturates arises from repeated administration of a barbiturate or agent with barbiturate-like effect on a continuous basis, generally in amounts exceeding therapeutic dose levels. The characteristics of drug dependence to barbiturates include: (a) a strong desire or need to continue taking the drug, (b) a tendency to increase the dose, (c) a psychic dependence on the effects of the drug related to subjective and individual appreciation of those effects and (d) a physical dependence on the effects of the drug requiring its presence for maintenance of homeostasis and resulting in a definite, characteristic and self-limited abstinence syndrome when the drug is withdrawn.

Individuals subject to barbiturate abuse and dependence include alcoholics and opiate abusers as well as other sedative-hypnotics and amphetamine abusers.

Treatment of barbiturate dependence consists of cautious and gradual withdrawal of the drug. Barbiturate-dependent patients can be withdrawn by using a number of different withdrawal regimens. In all cases, withdrawal takes an extended period of time. One method involves substituting a 30 mg dose of phenobarbital for each 100 to 200 mg dose of barbiturate that the patient has been taking. The total daily amount of phenobarbital is then administered in 3 to 4 divided doses, not to exceed 600 mg daily. Should signs of withdrawal occur on the first day of treatment, a loading dose of 100 to 200 mg of phenobarbital may be administered IM in addition to the oral dose. After stabilization on phenobarbital, the total daily dose is decreased by 30 mg a day as long as withdrawal is proceeding smoothly. If withdrawal symptoms appear, dosage is maintained at that level or increased slightly until symptoms disappear. A modification of this regimen involves initiating treatment at the patient’s regular dosage level and decreasing the daily dosage by 10 percent if tolerated by the patient. The symptoms of withdrawal can be severe and may cause death. Minor withdrawal symptoms (e.g., anxiety, muscle twitching, tremors, nausea, etc.) may appear 8-12 hours after the last dose of a barbiturate. Major withdrawal symptoms (convulsions and delirium) may occur within 16 hours and last up to five days after abrupt cessation of the barbiturate. The intensity of withdrawal symptoms gradually declines over a period of two weeks.

Infants physically dependent on barbiturates may be given phenobarbital 3 to 10 mg/kg/day. After withdrawal symptoms (hyperactivity, disturbed sleep, tremors, hyperreflexia) are relieved, the dosage of phenobarbital should be gradually decreased and completely withdrawn over a 2-week period.

OVERDOSAGE

The toxic dose of barbiturates varies considerably. Barbiturate intoxication may be confused with alcoholism, bromide intoxication and various neurological disorders.

For sedation, therapeutic blood levels of phenobarbital range from 5-40 µg/mL; the lethal blood level is greater than 80 µg/mL and usually ranges from 100-200 µg/mL.

Acute overdosage with barbiturates is manifested by CNS and respiratory depression which may progress to Cheyne-Stokes respiration, areflexia, constriction of the pupils to a slight degree (though in severe poisoning, they may show paralytic dilation), oliguria, tachycardia, hypotension, lowered body temperature and coma. Typical shock syndrome (apnea, circulatory collapse, respiratory arrest and death) may occur.

In extreme overdose, all electrical activity in the brain may cease, in which case a “flat” EEG normally equated with clinical death cannot be accepted. This effect is fully reversible unless hypoxic damage occurs. Consideration should be given to the possibility of barbiturate intoxication even in situations that appear to involve trauma.

Complications such as pneumonia, pulmonary edema, cardiac arrhythmias, congestive heart failure and renal failure may occur. Uremia may increase CNS sensitivity to barbiturates if renal function is impaired. Differential diagnosis should include hypoglycemia, head trauma, cerebrovascular accidents, convulsive states and diabetic coma. To obtain up-to-date information about the treatment of overdosage, a good resource is your certified Regional Poison Control Center. Telephone numbers of certified poison control centers are listed in the Physicians’ Desk Reference (PDR). In managing overdosage, consider the possibility of multiple drug overdose, interaction among drugs and the unusual drug kinetics in your patient.

Treatment of overdosage is mainly supportive and consists of the following:

1. Maintenance of an adequate airway, with assisted respiration and oxygen administration as necessary.
2. Monitoring of vital signs and fluid balance.
3. Fluid therapy and other standard treatment for shock, if needed.
4. If renal function is normal, forced diuresis may aid in the elimination of the barbiturate. Alkalinization of the urine increases renal excretion of phenobarbital.
5. Although not recommended as a routine procedure, hemodialysis may be used in severe barbiturate intoxication or if the patient is anuric or in shock. Hemoperfusion through an anion-exchange resin or activated charcoal has been successful. Peritoneal dialysis is significantly less effective in removing barbiturates.
6. Patient should be rolled from side to side every 30 minutes.
7. Antibiotics should be given if pneumonia is suspected.
8. Appropriate nursing care to prevent hypostatic pneumonia, decubiti, aspiration and other complications of patients with altered states of consciousness.
9. The use of analeptic agents is not recommended.

DOSAGE AND ADMINISTRATION

Dosages of barbiturates must be individualized with full knowledge of their particular characteristics and recommended rates of administration. Factors to consider are the patient’s age, weight and condition.

Suggested doses of phenobarbital sodium for specific indications follow:

Pediatric Dosage

Recommended by the American Academy of Pediatrics (intended as a guide)

Preoperative Sedation: 1 to 3 mg/kg IM or IV

Anticonvulsion: 4 to 6 mg/kg/day for 7 to 10 days to blood level of 10 to 15 mcg/mL or 10 to 15 mg/kg/day IM or IV

Status Epilepticus: 15 to 20 mg/kg over 10 to 15 minutes IV

Adult Dosage

(intended as a guide)

Daytime Sedation: 30 to 120 mg daily in 2 to 3 divided doses IM or IV

Bedtime Hypnosis: 100 to 320 mg IM or IV

Preoperative Sedation: IM only — 100 to 200 mg 60 to 90 minutes before surgery

Acute Convulsions: 20 to 320 mg IM or IV, repeated in 6 hours as necessary

Parenteral routes should be used only when oral administration is impossible or impractical.

Intramuscular injection of the sodium salts of barbiturates should be made deeply into a large muscle and a volume of 5 mL should not be exceeded at any one site because of possible tissue irritation. Injection into or near peripheral nerves may result in permanent neurological deficit. After intramuscular injection of a hypnotic dose, the patient’s vital signs should be monitored.

Subcutaneous administration is not recommended (see CONTRAINDICATIONS).

Intravenous Administration

Intravenous injection is restricted to conditions in which other routes are not feasible, either because the patient is unconscious (as in cerebral hemorrhage, eclampsia or status epilepticus), or because the patient resists (as in delirium) or because prompt action is imperative. Slow IV injection is essential, and patients should be carefully observed during administration. This requires that blood pressure, respiration and cardiac function be maintained, vital signs be recorded and equipment for resuscitation and artificial ventilation be available. The rate of intravenous injection for adults should not exceed 60 mg/min for phenobarbital sodium.

When given intravenously, do not use small veins, such as those on the dorsum of the hand or wrist. Preference should be given to a larger vein to minimize the risk of irritation with the possibility of resultant thrombosis. Avoid administration into varicose veins because circulation there is retarded. Inadvertent injection into or adjacent to an artery has resulted in gangrene requiring amputation of an extremity or a portion thereof. Careful technique, including aspiration, is necessary to avoid inadvertent intraarterial injection. (See below.)

Treatment of Adverse Effects Due to Inadvertent Error in Administration

Extravasation into subcutaneous tissues causes tissue irritation. This may vary from slight tenderness and redness to necrosis. Recommended treatment includes the application of moist heat and the injection of 0.5% procaine solution into the affected area.

Intraarterial injection of any barbiturate must be avoided. The accidental intraarterial injection of a small amount of the solution may cause spasm and severe pain along the course of the artery. The injection should be terminated if the patient complains of pain or if other indications of accidental intraarterial injection occur, such as a white hand with cyanosed skin or patches of discolored skin and delayed onset of hypnosis.

The consequences of intraarterial injection of phenobarbital can vary from transient pain to gangrene. It is not possible to formulate strict rules for management of such accidents. The following procedures have been suggested: 1) release of the tourniquet or restrictive garments to permit dilution of injected drug, 2) relief of arterial spasm by injecting 10 mL of a 1% procaine solution into the artery and, if considered necessary, brachial plexus block, 3) prevention of thrombosis by early anticoagulant therapy and 4) supportive treatment.

Anticonvulsant Use

A therapeutic anticonvulsant level of phenobarbital in the serum is 10 to 25 µg/mL. To achieve the blood levels considered therapeutic in children, higher per-kilogram dosages are generally necessary for phenobarbital and most other anticonvulsants. In children and infants, phenobarbital at loading doses of 15 to 20 mg/kg produces blood levels of about 20 µg/mL shortly after administration.

In status epilepticus, it is imperative to achieve therapeutic blood levels of a barbiturate (or other anticonvulsants) as rapidly as possible. When administered intravenously, phenobarbital sodium may require 15 minutes or more to attain peak concentrations in the brain. If phenobarbital sodium is injected continuously until the convulsions stop, the brain concentration will continue to rise and can eventually exceed that required to control the seizures. Because a barbiturate-induced depression may occur along with a postictal depression once the seizures are controlled, it is important, therefore, to use the minimal amount required and to wait for the anticonvulsant effect to develop before administering a second dose.

Phenobarbital has been used in the treatment and prophylaxis of febrile seizures. However, it has not been established that prevention of febrile seizures influences the subsequent development of epilepsy.

Special Patient Population

Dosage should be reduced in the elderly or debilitated because these patients may be more sensitive to barbiturates. Dosage should be reduced for patients with impaired renal function or hepatic disease.

Parenteral drug products should be inspected visually for particulate matter and discoloration prior to administration, whenever solution and container permit.

HOW SUPPLIED

Phenobarbital Sodium Injection, USP is available in the following:

65 mg/mL, 1 mL vials packaged in 10s (NDC 54288-136-10) and 25s (NDC 54288-136-25)

130 mg/mL, 1 mL vials packaged in 10s (NDC 54288-137-10) and 25s (NDC 54288-137-25)

Storage

Store at 20°-25°C (68°-77°F), excursions permitted to 15°-30°C (59°-86°F) [See USP Controlled Room Temperature].

Do not use if solution is discolored or contains a precipitate.

Contains no preservatives.

To report SUSPECTED ADVERSE REACTIONS, contact BPI Labs, LLC at 727-471-0850, or the FDA at 1-800-FDA-1088 or www.fda.gov/medwatch.

For Product Inquiry call 727-471-0850.

Manufactured by:

BPI Labs, LLC

12393 Belcher Rd S, Ste 450,

Largo, FL USA 33773 R-2302

LI28I-29I

PRINCIPAL DISPLAY PANEL

Phenobarbital Sodium Injection, USP
65 mg/mL
1 mL Vial
NDC 54288-136-01

Phenobarbital Sodium Injection, USP
65 mg/mL
10 x 1 mL Vials
NDC 54288-136-10

Phenobarbital Sodium Injection, USP
65 mg/mL
25 x 1 mL Vials
NDC 54288-136-25

PRINCIPAL DISPLAY PANEL

Phenobarbital Sodium Injection, USP
130 mg/mL
1 mL Vial
NDC 54288-137-01

Phenobarbital Sodium Injection, USP
130 mg/mL
10 x 1 mL Vials
NDC 54288-137-10

Phenobarbital Sodium Injection, USP
130 mg/mL
25 x 1 mL Vials
NDC 54288-137-25